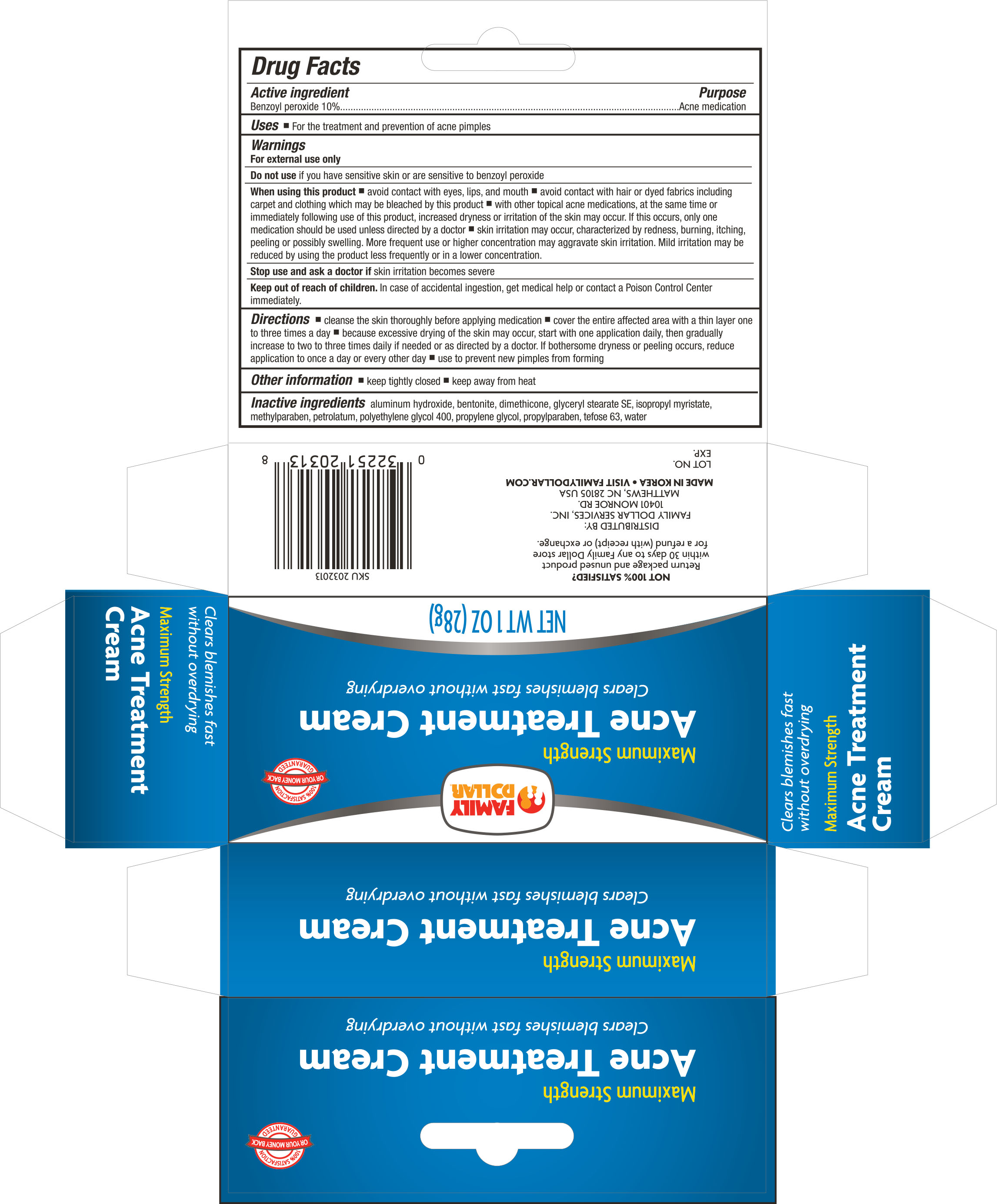 DRUG LABEL: FAMILY DOLLAR ACNE TREATMENT
NDC: 55319-203 | Form: CREAM
Manufacturer: FAMILY DOLLAR
Category: otc | Type: HUMAN OTC DRUG LABEL
Date: 20160919

ACTIVE INGREDIENTS: BENZOYL PEROXIDE 10 g/100 g
INACTIVE INGREDIENTS: ALUMINUM HYDROXIDE; BENTONITE; DIMETHICONE; GLYCERYL STEARATE SE; ISOPROPYL MYRISTATE; METHYLPARABEN; PETROLATUM; POLYETHYLENE GLYCOL 400; PROPYLENE GLYCOL; PROPYLPARABEN; WATER

Active ingredient Purpose

Benzoyl Peroxide 10%......................................................................Acne medications

Uses

- for the treatment and prevention of acne pimples

Warnings

For external use only

Do not use if you have sensitive skin or are sensitive to benzoyl peroxide

When using this product

- avoid contact with eyes, lips and mouth
- avoid contact with hair or dyed fabrics including carpet and clothing which may be bleached by this product
- with other tropical acne medications, at the same time or immediately following use of this product, increased dryness or irritation of the skin may occur. If this occurs, only one medications should be use unless directed by a doctor
- skin irritation may occur, characterized by redness, burning, itching, peeling or possibly swelling. More frequent use or concentration may aggravate skin irritation. Mild irritation may be reduced by using the product less frequently or in a lower concentration.

Stop use and ask a doctor if skin irritation becomes severe

Keep out of reach of children. In case of accidental ingestion, get medical help or contact a Poison Control Center immediately.

Directions

- cleanse the skin thoroughly before applying medication
- cover the entire affected area with a thin layer one to three times a day
- because excessive drying of the skin may occur, start with one application daily, then gradually increase to two to three times daily if needed or as directed by a doctor. If bothersome dryness or peeling occurs, reduce application to once a day or every other day
- use to prevent new pimples from forming

Other information

- keep tightly closed
- keep away from heat

Inactive ingredients

aluminum hydroxide, betonite, dimethicone, glyceryl, stearate SE, isopropyl myristate, methylparaben, petrolatum, polyethylene glycol 400, propylene glycol, propylpraben, tefose 63, water

DOSAGE AND ADMINISTRATION

Distributed By:

Family Dollar Services, Inc.
10401 Monroe Road
Matthews, NC 28105 USA
Made in Korea